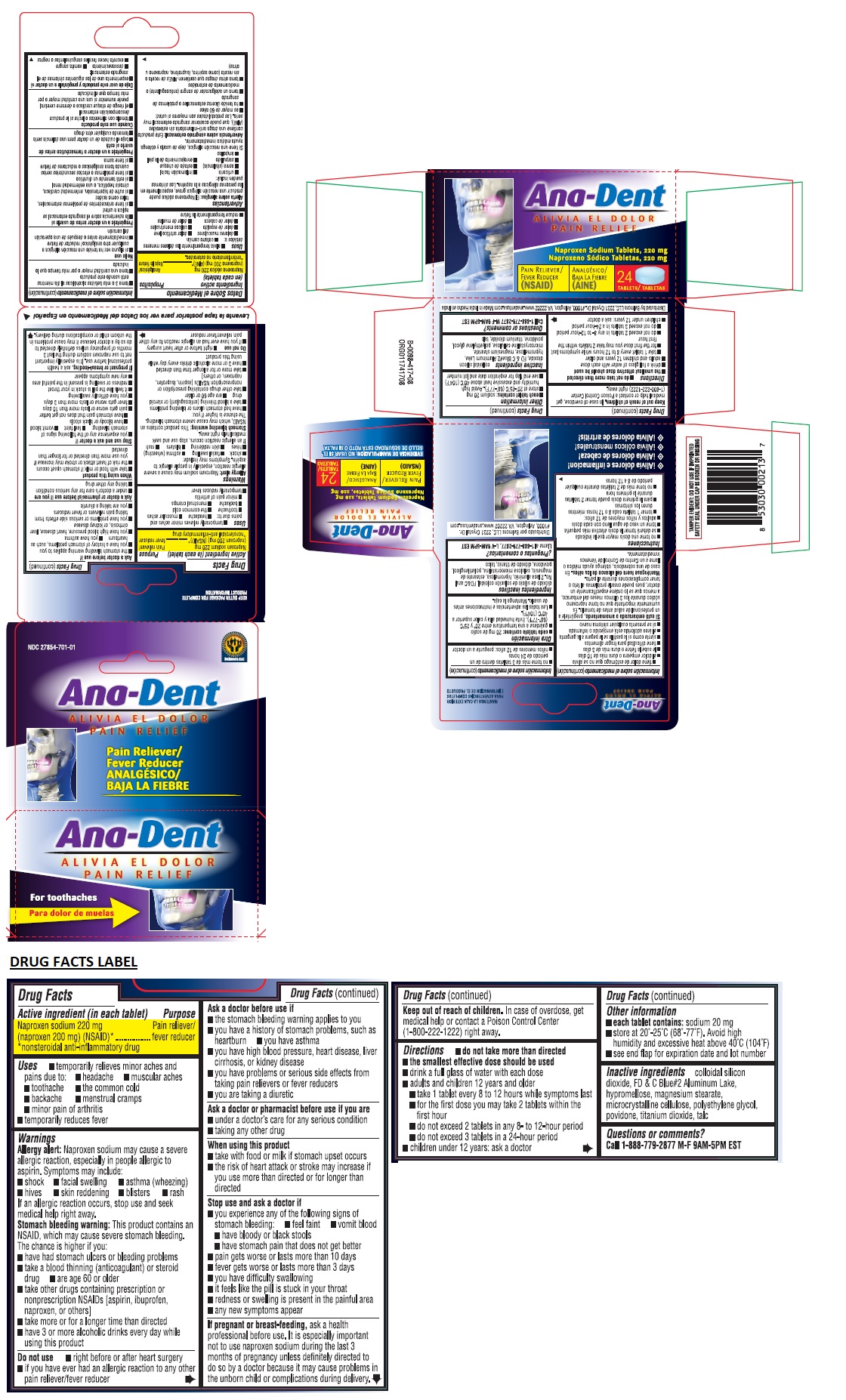 DRUG LABEL: Ana-Dent PAIN RELIEF
NDC: 27854-701 | Form: TABLET, FILM COATED
Manufacturer: Belmora LLC
Category: otc | Type: HUMAN OTC DRUG LABEL
Date: 20200518

ACTIVE INGREDIENTS: NAPROXEN SODIUM 220 mg/1 1
INACTIVE INGREDIENTS: SILICON DIOXIDE; FD&C BLUE NO. 2; HYPROMELLOSE 2910 (5 MPA.S); MAGNESIUM STEARATE; MICROCRYSTALLINE CELLULOSE; POLYETHYLENE GLYCOL 8000; POVIDONE K30; TITANIUM DIOXIDE; TALC

Ana-Dent PAIN RELIEF

Active ingredient (in each tablet)

Naproxen sodium 220 mg (naproxen 200 mg) (NSAID)*

*nonsteroidal anti-inflammatory drug

Purpose

Pain reliever/ fever reducer

INDICATIONS AND USAGE

Uses ■ temporarily relieves minor aches and pain due to: ■ headache ■ muscular aches ■ toothache ■ the common cold ■ backache ■ menstrual cramps ■ minor pain of arthritis

■ temporarily reduces fever

Warnings

Allergy alert: Naproxen sodium may cause a severe allergic reaction, especially in people allergic to aspirin. Symptoms may include: ■ shock ■ facial swelling ■ asthma (wheezing) ■ hives ■ skin reddening ■ blisters ■ rash

If an allergic reaction occurs, stop use and seek medical help right away.

Stomach bleeding warning: This product contains an NSAID, which may cause severe stomach bleeding. The chance is higher if you

■ have had stomach ulcers or bleeding problems

■ take blood thinning (anticoagulant) or steroid drug

■ are age 60 or older

■ take other drugs containing prescription or nonprescription NSAIDs [aspirin, ibuprofen, naproxen, or others]

■ take more or for a longer time than directed

■ have 3 or more alcoholic drinks every day while using this product.

Do not use ■ right before or after heart surgery ■ if you have ever had an allergic reaction to any other pain reliever/fever reducer

Ask a doctor before use if

■ the stomach bleeding warning applies to you

■ you have a history of stomach problems, such as heartburn

■ you have asthma

■ you have high blood pressure, heart disease, liver cirrhosis or kidney disease

■ you have a problems or serious side effects from taking pain relievers or fever reducers

■ you are taking a diuretic

Ask a doctor or pharmacist before use if you are

■ under a doctor's care for any serious condition

■ taking any other drug

When using this product

■ take with food or milk if stomach upset occurs

■ the risk of heart attack or stroke may increase if you use more than directed or for longer than directed

Stop use and ask a doctor if

■ you experience any of the following signs of stomach bleeding: ■ feel faint ■ vomit blood ■ have bloody or black stools ■ have stomach pain that does not get better

■ pain gets worse or lasts more than 10 days

■ fever gets worse or lasts more than 3 days

■ you have difficulty swallowing

■ it feels like the pill is stuck in your throat

■ redness or swelling is present in the painful area

■ any new symptoms appear

If pregnant or breast-feeding, ask a health professional before use. It is especially important not to use naproxen sodium during the last 3 months of pregnancy unless definitely directed to do so by a doctor because it may cause problems in the unborn child or complications during delivery.

Keep out of reach of children. In case of overdose, get medical help or contact a Poison Control Center (1-800-222-1222) right away.

DOSAGE AND ADMINISTRATION

Directions ■ do not take more than directed

■ the smallest effective dose should be used

■ drink a full glass of water with each dose

■ adults and children 12 years and older

■ take 1 tablet every 8 to12 hours while symptoms last
■ for the first dose, you may take 2 tablets within the first hour
■ do not exceed 2 tablets in any 8-to 12-hour period
■ do not exceed 3 tablets in a 24-hour period

■ children under 12 years: ask a doctor

Other information

■ each tablet contains: sodium 20 mg

■ store at 20°-25°C (68°-77°F). Avoid high humidity and excessive heat above 40°C (104°F)

■ see end flap for expiration date and lot number

INACTIVE INGREDIENT

Inactive ingredients colloidal silicon dioxide, FD & C Blue#2 Aluminum Lake, hypromellose, magnesium stearate, microcrystalline cellulose, polyethylene glycol, povidone, titanium dioxide, talc

Questions or comments?

Call 1-888-779-2877 M-F 9AM-5PM EST

For toothaches

KEEP OUTER PACKAGE FOR COMPLETE PRODUCT INFORMATION

Distributed by Belmora LLC, 2011 Crystal Dr. Suite 400 Arlington, VA 22202

www.anadentusa.com

Made in India

TAMPER EVIDENT: DO NOT USE IF IMPRINTED SAFETY SEAL UNDER CAP IS BROKEN OR MISSING